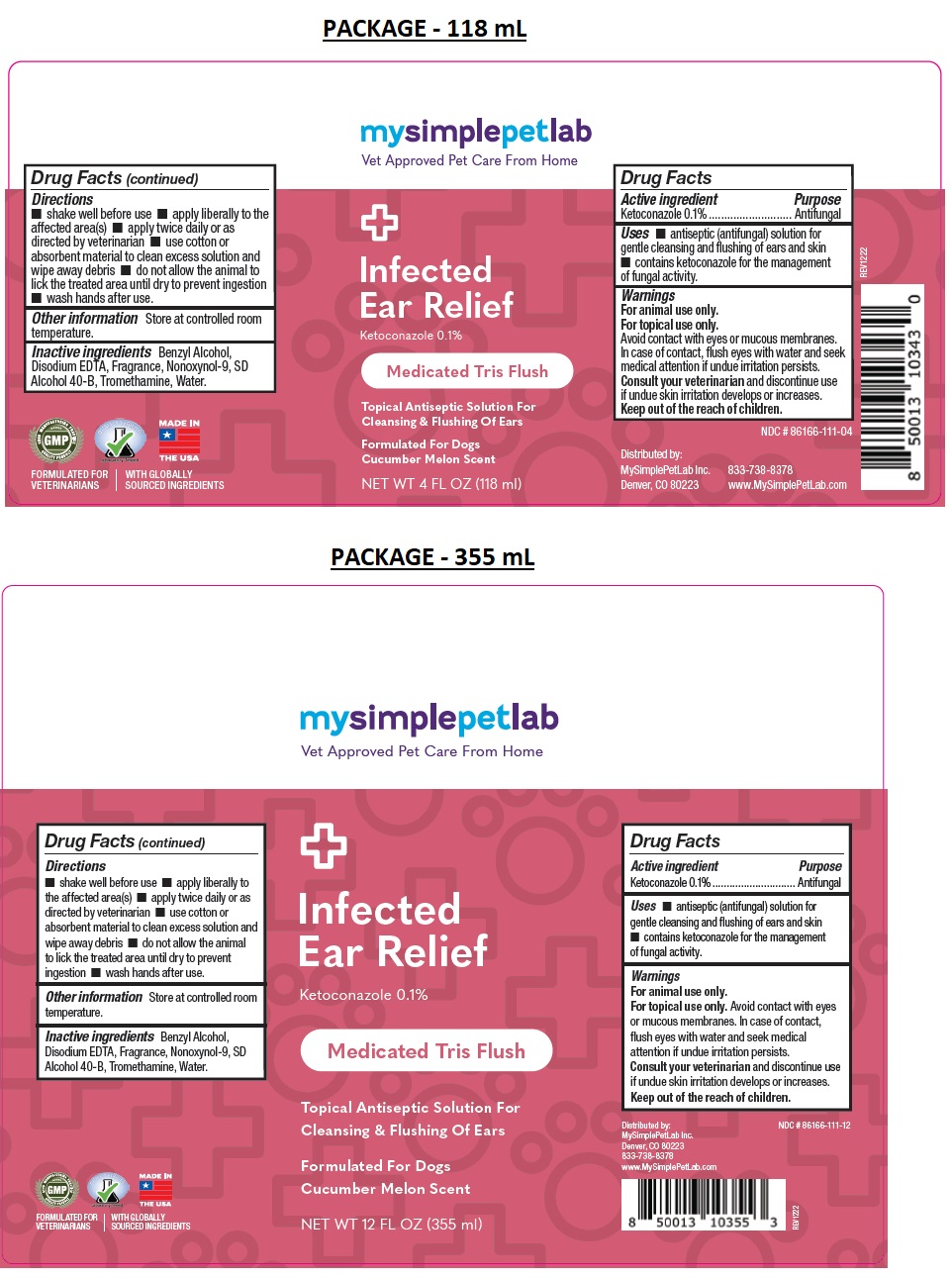 DRUG LABEL: MySimplePetLab Infected Ear Relief
NDC: 86166-111 | Form: SOLUTION
Manufacturer: Mysimplepetlab Inc
Category: animal | Type: OTC ANIMAL DRUG LABEL
Date: 20221201

ACTIVE INGREDIENTS: KETOCONAZOLE 0.1 g/100 mL
INACTIVE INGREDIENTS: BENZYL ALCOHOL; EDETATE DISODIUM ANHYDROUS; NONOXYNOL-9; ALCOHOL; TROMETHAMINE; WATER

mysimplepetlab Infected Ear Relief

Active ingredient

Ketoconazole 0.1%

Purpose

Antifungal

Uses

• antiseptic (antifungal) solution for gentle cleansing and flushing of ears and skin • contains ketoconazole for the management of fungal activity.

Warnings

For animal use only.

For topical use only. Avoid contact with eyes or mucous membranes. In case of contact, flush eyes with water and seek medical attention if undue irritation persists.

Consult your veterinarian and discontinue use if undue skin irritation develops or increases.

Keep out of the reach of children.

Directions

• shake well before use • apply liberally to the affected area(s) • apply twice daily or as directed by veterinarian • use cotton or absorbent material to clean excess solution and wipe away debris • do not allow the animal to lick the treated area until dry to prevent ingestion • wash hands after use.

Other information

Store at controlled room temperature.

Inactive ingredients

Benzyl Alcohol, Disodium EDTA, Fragrance, Nonoxynol-9, SD Alcohol 40-B, Tromethamine, Water.

Vet Approved Pet Care From Home

Medicated Tris Flush

Topical Antiseptic Solution For Cleansing & Flushing Of Ears

Formulated For Dogs

Cucumber Melon Scent

MADE IN THE USA

FORMULATED FOR VETERINARIANS | WITH GLOBALLY SOURCED INGREDIENTS

Distributed by:
MySimplePetLab Inc.
Denver, CO 80223
833-738-8378
www.MySimplePetLab.com